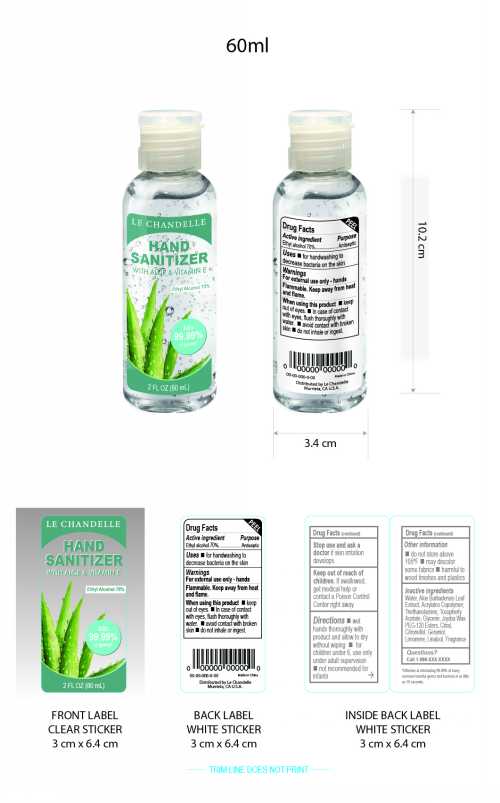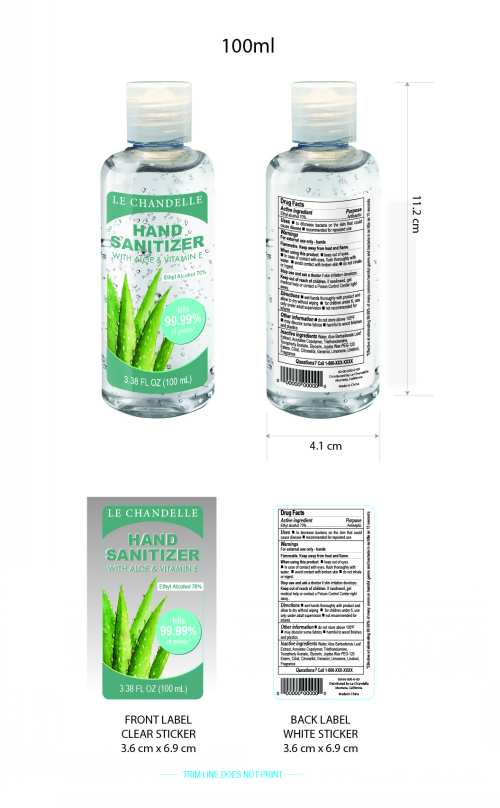 DRUG LABEL: Hand Sanitizer
NDC: 78025-001 | Form: GEL
Manufacturer: Le Chandelle
Category: otc | Type: HUMAN OTC DRUG LABEL
Date: 20200517

ACTIVE INGREDIENTS: ALCOHOL 75 mL/100 mL
INACTIVE INGREDIENTS: .ALPHA.-TOCOPHEROL ACETATE; ALOE VERA LEAF; BUTYL ACRYLATE/METHYL METHACRYLATE/METHACRYLIC ACID COPOLYMER (18000 MW); WATER; CITRAL; LINALOOL, (+/-)-; GLYCERIN; .BETA.-CITRONELLOL, (R)-; GERANIOL; LIMONENE, (+)-; TROLAMINE

Hand Sanitizer

Active Ingredient

Ethyl alcohol 70%

Purpose

Antiseptic

Uses

- for handwashing to decrease bacteria on the skin.

Warnings

For external use only-hands Flammable.Keep away from heat and flame.

DO NOT USE

- if skin irritation develops

Stop use and ask a doctor

if skin irritation develops

When using this product.

- Keep out of eyes.
- In case of contact with eyes,flush thoroughly with water.
- avoid contact with broken skin.
- do not inhale or ingest.

Keep out of reach of children

- If swallowed,get medical help or contact a Poison Control Center right away.

Directions

wet

hands thoroughly with product and allow to dry without wiping

for children under 6,use only under adult supervision

not recommended for infants.

Other information

- do not store above105℉
- may discolor some fabrics
- harmful to wood finishes and plastics

Inactive ingredients

Water,Aloe Barbadensis Leaf Extract, Acrylates Copolymer,Triethanolamine,Tocopherly Acetate,Glycerin,

Jojoba Wax PEG-120 Esters,Citral,Citronellol,Geraniol,Limonene,Linalool,Fragrance